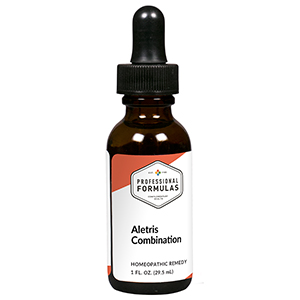 DRUG LABEL: Aletris Combination
NDC: 63083-9203 | Form: LIQUID
Manufacturer: Professional Complementary Health Formulas
Category: homeopathic | Type: HUMAN OTC DRUG LABEL
Date: 20190815

ACTIVE INGREDIENTS: ALETRIS FARINOSA ROOT 4 [hp_X]/29.5 mL; ANAMIRTA COCCULUS FRUIT 4 [hp_X]/29.5 mL; IRON 6 [hp_X]/29.5 mL; FERRIC CATION 6 [hp_X]/29.5 mL; FERROSOFERRIC PHOSPHATE 6 [hp_X]/29.5 mL; FERROUS CATION 6 [hp_X]/29.5 mL; CHAMAELIRIUM LUTEUM ROOT 6 [hp_X]/29.5 mL; SODIUM CHLORIDE 6 [hp_X]/29.5 mL; PICRIC ACID 6 [hp_X]/29.5 mL; SEPIA OFFICINALIS JUICE 6 [hp_X]/29.5 mL; QUININE ARSENITE 8 [hp_X]/29.5 mL; POTASSIUM CARBONATE 8 [hp_X]/29.5 mL
INACTIVE INGREDIENTS: ALCOHOL; WATER

R203

ACTIVE INGREDIENTS

Aletris farinosa 4X
Cocculus indicus 4X
Ferrum metallicum 6X
Ferrum muriaticum 6X
Ferrum phosphoricum 6X
Ferrum sulphuricum 6X
Helonias dioica 6X
Natrum muriaticum 6X
Picricum acidum 6X
Sepia 6X
Chininum arsenicosum 8X
Kali carbonicum 8X

QUESTIONS

Professional Formulas

PO Box 2034 Lake Oswego, OR 97035

INDICATIONS

For the temporary relief of exhaustion, debility, weakness, or occasional headache.*

PURPOSE

*Claims based on traditional homeopathic practice, not accepted medical evidence. Not FDA evaluated.

WARNINGS

In case of overdose, get medical help or contact a poison control center right away.

Keep out of the reach of children.

PREGNANCY OR BREAST FEEDING

If pregnant or breastfeeding, ask a healthcare professional before use.

DIRECTIONS

Place drops under tongue 30 minutes before/after meals. Adults and children 12 years and over: Take 10 drops up to 3 times per day. Consult a physician for use in children under 12 years of age.

OTHER INFORMATION

Tamper resistant. If seal is broken, do not use. After opening, close container tightly and store at room temperature away from heat.

INACTIVE INGREDIENTS

40% ethanol, purified water.

LABEL

Est 1985

Professional Formulas

Complementary Health

Aletris Combination

Homeopathic Remedy

1 FL. OZ. (29.5 mL)